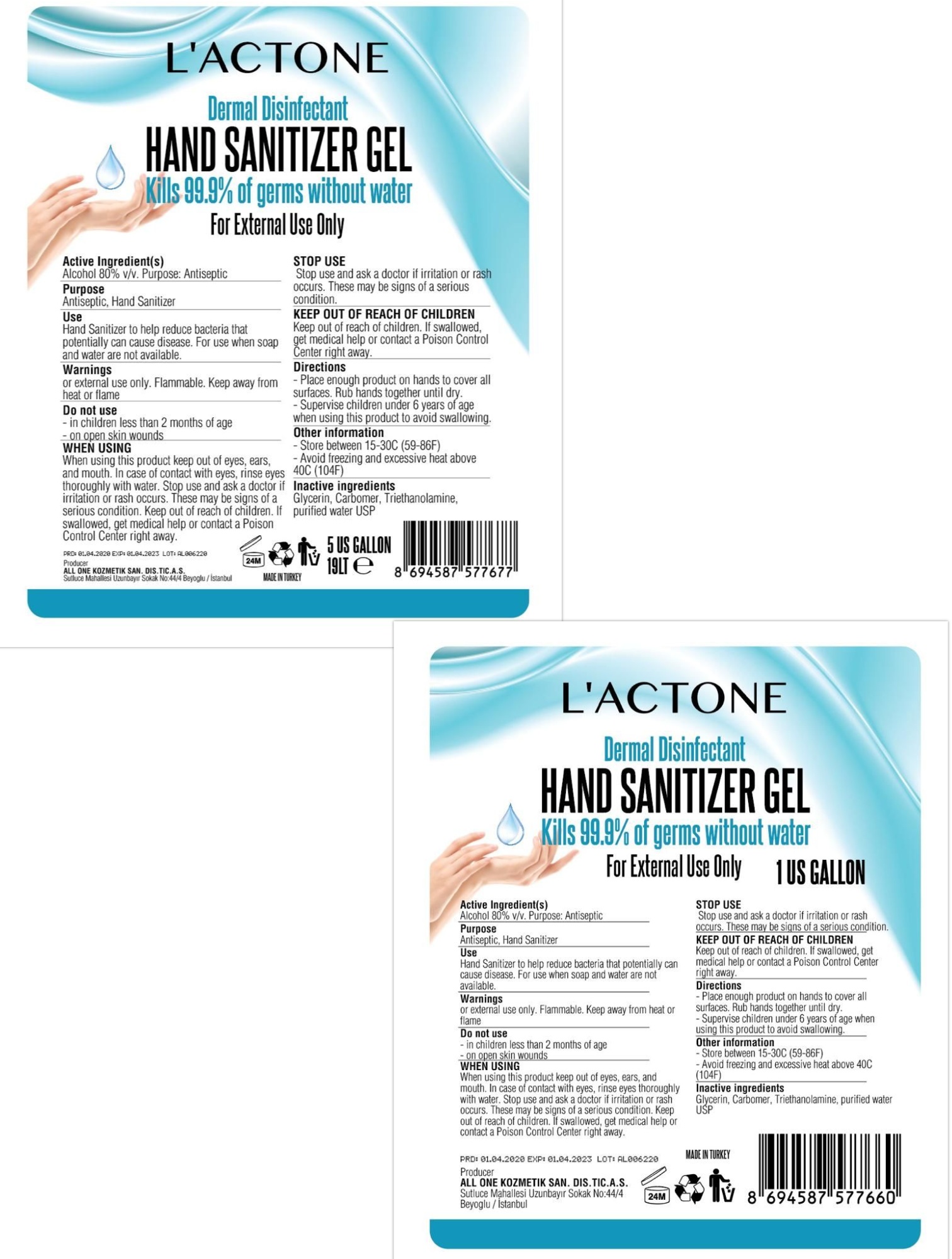 DRUG LABEL: LACTONE HAND SANITIZER
NDC: 75348-606 | Form: GEL
Manufacturer: ALL ONE KOZMETIK SANAYI DIS TICARET ANONIM SIRKETI
Category: otc | Type: HUMAN OTC DRUG LABEL
Date: 20200715

ACTIVE INGREDIENTS: ALCOHOL 80 mL/100 mL
INACTIVE INGREDIENTS: GLYCERIN; CARBOMER 980; WATER; TROLAMINE

Hand sanitizer 606 gallon

DESCRIPTION

L'ACTONE HAND SANITIZER GEL

Dermal Disinfectant

Active Ingredient(s)

Alcohol 80% v/v. Purpose: Antiseptic

Purpose

Antiseptic, Hand Sanitizer

Use

Hand Sanitizer to help reduce bacteria that potentially can cause disease. For use when soap and water are not available.

Warnings

For external use only. Flammable. Keep away from heat or flame

Do not use

- in children less than 2 months of age
- on open skin wounds

When using this product keep out of eyes, ears, and mouth. In case of contact with eyes, rinse eyes thoroughly with water.
Stop use and ask a doctor if irritation or rash occurs. These may be signs of a serious condition.
Keep out of reach of children. If swallowed, get medical help or contact a Poison Control Center right away.

Stop use and ask a doctor if irritation or rash occurs. These may be signs of a serious condition.

Keep out of reach of children. If swallowed, get medical help or contact a Poison Control Center right away.

Directions

- Place enough product on hands to cover all surfaces. Rub hands together until dry.
- Supervise children under 6 years of age when using this product to avoid swallowing.

Other information

- Store between 15-30C (59-86F)
- Avoid freezing and excessive heat above 40C (104F)

Inactive ingredients

glycerin, hydrogen peroxide, purified water USP

Package Label - Principal Display Panel

Producer

ALL ONE KOZMETIK SAN. DIS. TIC. A. S.

Sutluce Mahallesi

Uzunbayir Sokak No:44/4

Beyoglu/Istanbul

PRD: 01.04.2020

EXP: 01.04.2023

LOT: AL006220

MADE IN TURKEY

Dermal Disinfectant

HAND SANITIZER GEL

Kills 99.9% of germs without water

For External Use Only